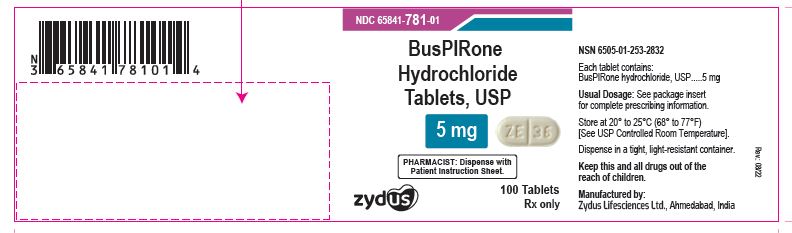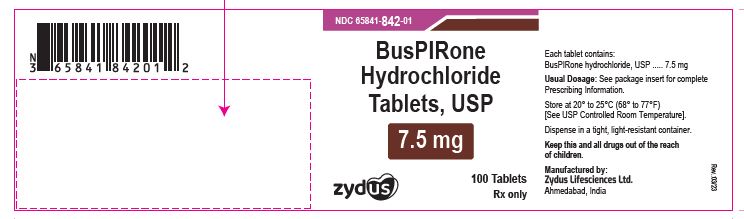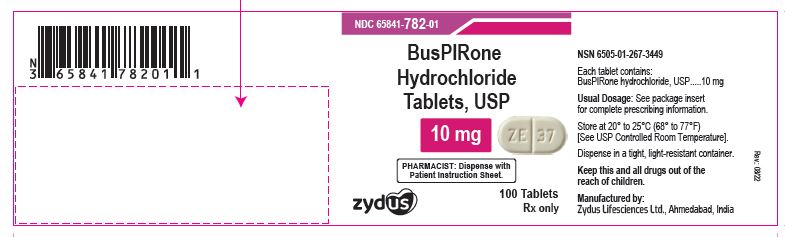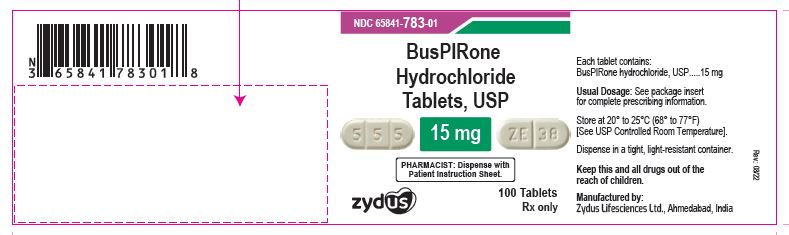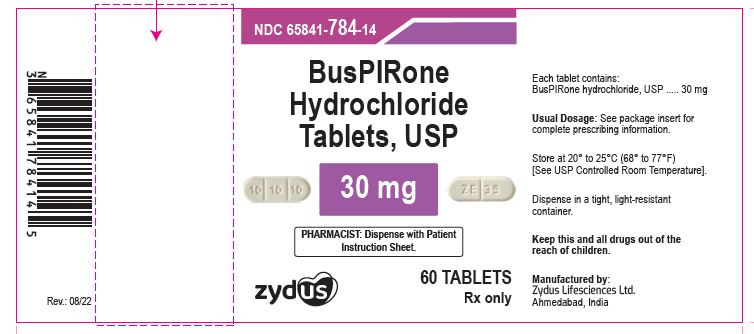 DRUG LABEL: buspirone hydrochloride
NDC: 65841-781 | Form: TABLET
Manufacturer: Zydus Lifesciences Limited
Category: prescription | Type: HUMAN PRESCRIPTION DRUG LABEL
Date: 20251224

ACTIVE INGREDIENTS: BUSPIRONE HYDROCHLORIDE 5 mg/1 1
INACTIVE INGREDIENTS: SILICON DIOXIDE; LACTOSE MONOHYDRATE; MAGNESIUM STEARATE; CELLULOSE, MICROCRYSTALLINE; SODIUM STARCH GLYCOLATE TYPE A POTATO

Buspirone Hydrochloride Tablets

PACKAGE LABEL.PRINCIPAL DISPLAY PANEL

NDC 65841-781-01 in bottle of 100 tablets

Buspirone Hydrochloride Tablets USP, 5 mg

Rx only

100 tablets

NDC 65841-842-01 in bottle of 100 tablets

Buspirone Hydrochloride Tablets USP, 7.5 mg

Rx only

100 tablets

NDC 65841-782-01 in bottle of 100 tablets

Buspirone Hydrochloride Tablets USP, 10 mg

Rx only

100 tablets

NDC 65841-783-01 in bottle of 100 tablets

Buspirone Hydrochloride Tablets USP, 15 mg

Rx only

100 tablets

NDC 65841-784-14 in bottle of 60 tablets

Buspirone Hydrochloride Tablets USP, 30 mg

Rx only

60 tablets